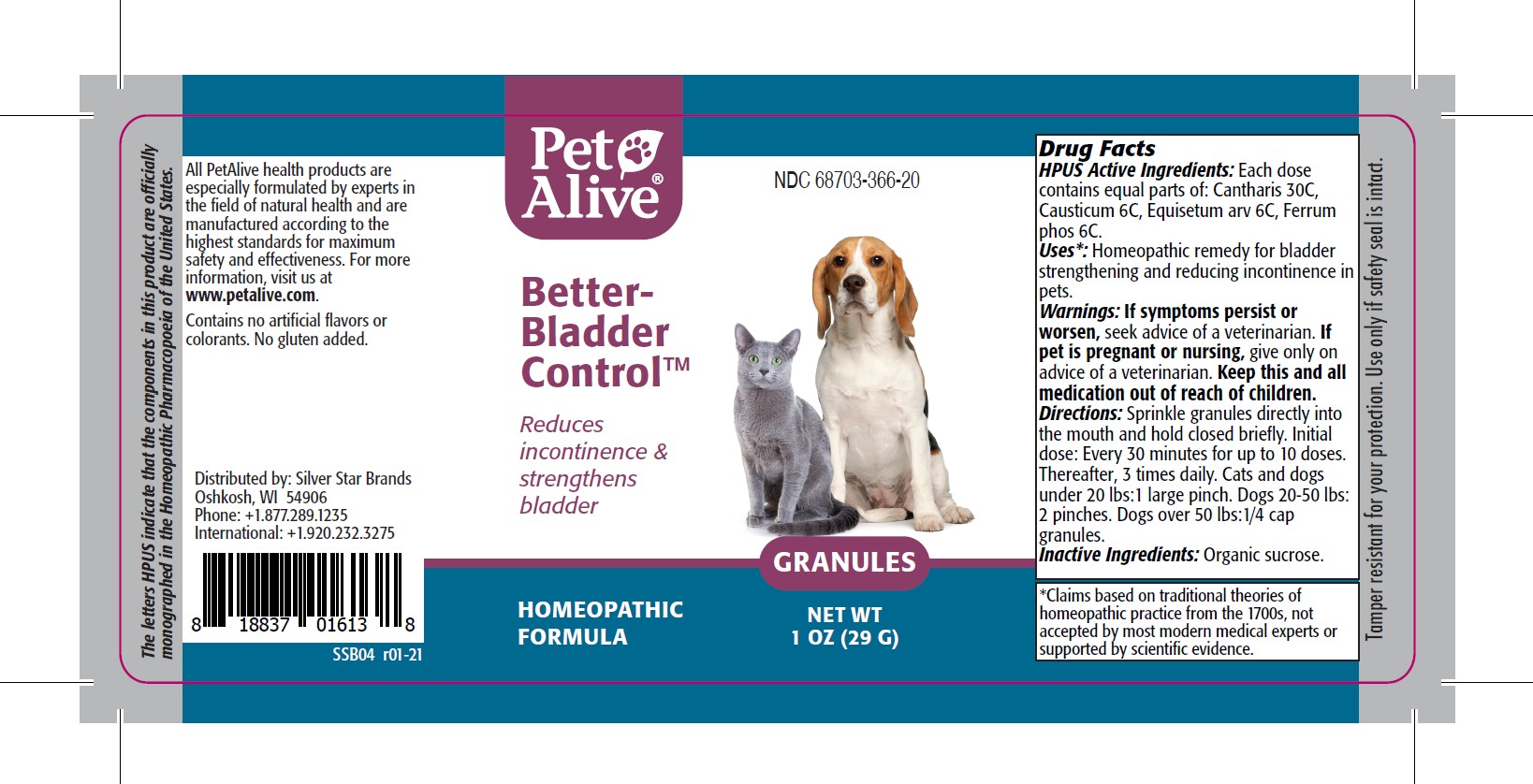 DRUG LABEL: PetAlive Better-Bladder Control
NDC: 68703-366 | Form: GRANULE
Manufacturer: SILVER STAR BRANDS
Category: homeopathic | Type: OTC ANIMAL DRUG LABEL
Date: 20251216

ACTIVE INGREDIENTS: LYTTA VESICATORIA 30 [hp_C]/20 mg; CAUSTICUM 6 [hp_C]/20 mg; EQUISETUM ARVENSE TOP     6 [hp_C]/20 mg; FERROSOFERRIC PHOSPHATE 6 [hp_C]/20 mg
INACTIVE INGREDIENTS: SUCROSE

PetAlive Better-Bladder Control

PURPOSE

Reduces incontinence and strengthens bladder

HPUS Active Ingredients:

Cantharis 30C
Causticum 6C
Equisetum arv 6C
Ferrum phos 6C

INDICATIONS AND USAGE

Uses: Homeopathic remedy for bladder strengthening and reducing incontinence in pets.

WARNINGS

Warning: If symptoms persist or worsen, seek advice of a veterinarian.

PREGNANCY OR BREAST FEEDING

If pet is pregnant or nursing, give only on advice of a veterinarian.

KEEP OUT OF REACH OF CHILDREN

Keep this and all medication out of reach of children

DOSAGE AND ADMINISTRATION

Directions: Sprinkle granules directly into the mouth and hold closed briefly. Initial dose: Every 30 minutes for up to 10 doses. Thereafter, 3 times daily. Cats and dogs under 20 lbs:1 large pinch. Dogs 20-50 lbs 2 pinches. Dogs over 50 lbs:1/4 cap granules.

Inactive Ingredients: Organic sucrose

INFORMATION FOR OWNERS/CAREGIVERS

The letters HPUS indicate that the components in this product are officially monographed in the Homeopathic Pharmacopoeia of the United States.

All PetAlive health products are especially formulated by experts in the field of natural health and are manufactured according to the highest standards for maximum safety and effectiveness. For more information, visit us at www.petalive.com.

Contains no artificial flavors or colorants. No gluten added.

Distributed by: Silver Star Brands
Oshkosh, WI 54906
Phone: +1.877.289.1235
International: +1.920.232.3275

STORAGE AND HANDLING

Tamper resistant for your protection. Use only if safety seal is intact.